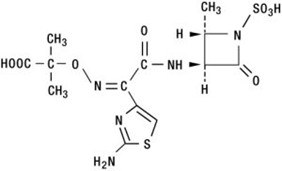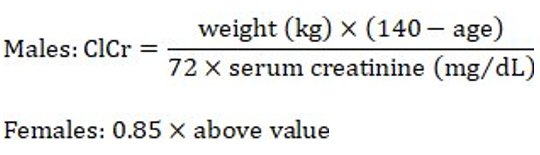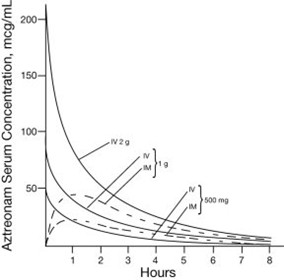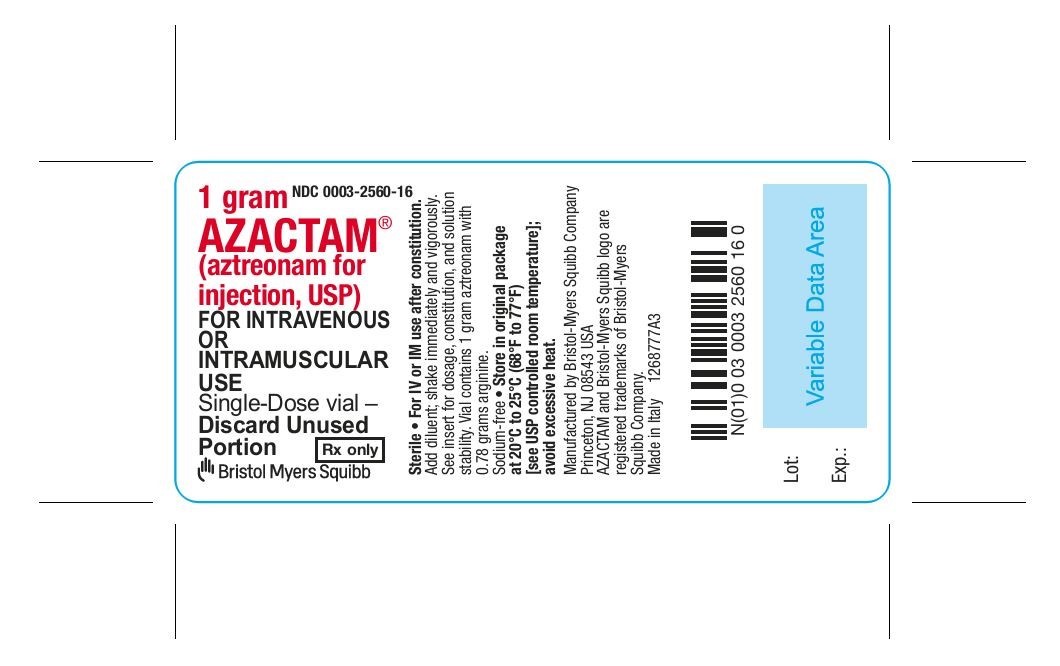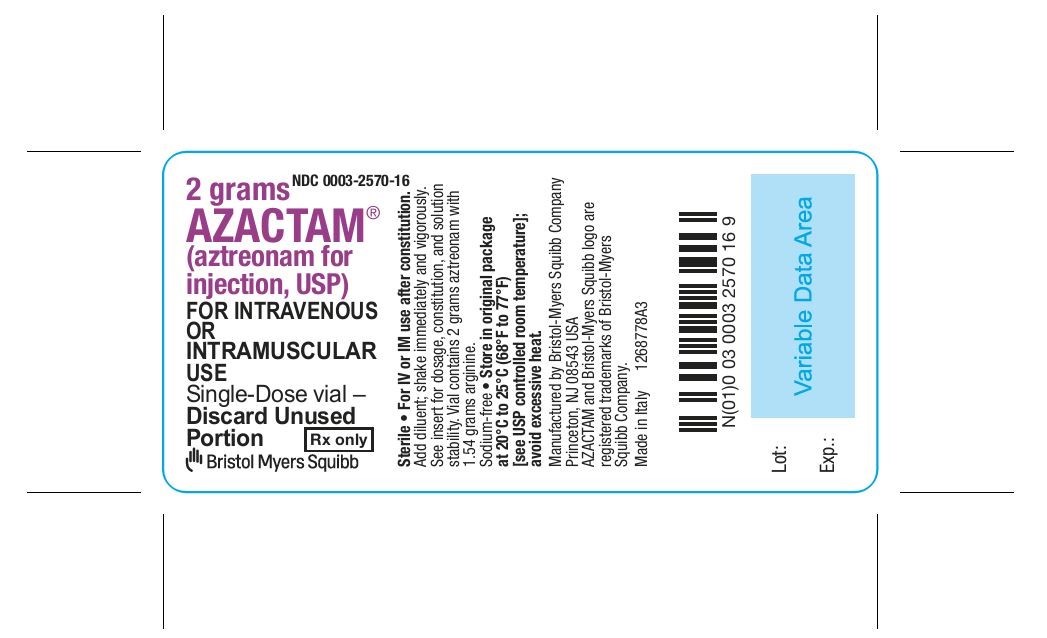 DRUG LABEL: AZACTAM
NDC: 0003-2560 | Form: INJECTION, POWDER, FOR SOLUTION
Manufacturer: E.R. Squibb & Sons, L.L.C.
Category: prescription | Type: HUMAN PRESCRIPTION DRUG LABEL
Date: 20251215

ACTIVE INGREDIENTS: aztreonam 1 g/1 1
INACTIVE INGREDIENTS: arginine 0.78 g/1 1

AZACTAM®

(aztreonam for injection, USP)

To reduce the development of drug-resistant bacteria and maintain the effectiveness of AZACTAM® and other antibacterial drugs, AZACTAM should be used only to treat or prevent infections that are proven or strongly suspected to be caused by bacteria.

DESCRIPTION

AZACTAM® (aztreonam for injection, USP) contains the active ingredient aztreonam, a monobactam. It was originally isolated from Chromobacterium violaceum. It is a synthetic bactericidal antibiotic.

The monobactams, having a unique monocyclic beta-lactam nucleus, are structurally different from other beta-lactam antibiotics (eg, penicillins, cephalosporins, cephamycins). The sulfonic acid substituent in the 1-position of the ring activates the beta-lactam moiety; an aminothiazolyl oxime side chain in the 3-position and a methyl group in the 4-position confer the specific antibacterial spectrum and beta-lactamase stability.

Aztreonam is designated chemically as (Z)-2-[[[(2-amino-4-thiazolyl)[[(2S,3S)-2-methyl-4-oxo-1-sulfo-3-azetidinyl]carbamoyl]methylene]amino]oxy]-2-methylpropionic acid.

Structural formula:

C13H17N5O8S2 MW 435.44

AZACTAM is a sterile, nonpyrogenic, sodium-free, white powder containing 0.78 grams arginine per 1 gram of aztreonam and 1.54 grams arginine per 2 grams of aztreonam. Following constitution, the product is for intramuscular or intravenous use. Aqueous solutions of the product have a pH in the range of 4.5 to 7.5.

CLINICAL PHARMACOLOGY

Single 30-minute intravenous infusions of 500 mg, 1 g, and 2 g doses of AZACTAM in healthy subjects produced aztreonam peak serum levels of 54 mcg/mL, 90 mcg/mL, and 204 mcg/mL, respectively, immediately after administration; at 8 hours, serum levels were 1 mcg/mL, 3 mcg/mL, and 6 mcg/mL, respectively (Figure 1). Single 3-minute intravenous injections of the same doses resulted in serum levels of 58 mcg/mL, 125 mcg/mL, and 242 mcg/mL at 5 minutes following completion of injection.

Serum concentrations of aztreonam in healthy subjects following completion of single intramuscular injections of 500 mg and 1 g doses are depicted in Figure 1; maximum serum concentrations occur at about 1 hour. After identical single intravenous or intramuscular doses of AZACTAM, the serum concentrations of aztreonam are comparable at 1 hour (1.5 hours from start of intravenous infusion) with similar slopes of serum concentrations thereafter.

FIGURE 1

The serum levels of aztreonam following single 500 mg or 1 g (intramuscular or intravenous) or 2 g (intravenous) doses of AZACTAM exceed the MIC90 for Neisseria sp., Haemophilus influenzae, and most genera of the Enterobacteriaceae for 8 hours (for Enterobacter sp., the 8-hour serum levels exceed the MIC for 80% of strains). For Pseudomonas aeruginosa, a single 2 g intravenous dose produces serum levels that exceed the MIC90 for approximately 4 to 6 hours. All of the above doses of AZACTAM result in average urine levels of aztreonam that exceed the MIC90 for the same pathogens for up to 12 hours.

When aztreonam pharmacokinetics were assessed for adult and pediatric patients, they were found to be comparable (down to 9 months old). The serum half-life of aztreonam averaged 1.7 hours (1.5-2.0) in subjects with normal renal function, independent of the dose and route of administration. In healthy subjects, based on a 70 kg person, the serum clearance was 91 mL/min and renal clearance was 56 mL/min; the apparent mean volume of distribution at steady-state averaged 12.6 liters, approximately equivalent to extracellular fluid volume.

In elderly patients, the mean serum half-life of aztreonam increased and the renal clearance decreased, consistent with the age-related decrease in creatinine clearance. The dosage of AZACTAM should be adjusted accordingly (see DOSAGE AND ADMINISTRATION: Renal Impairment in Adult Patients).

In patients with impaired renal function, the serum half-life of aztreonam is prolonged. (See DOSAGE AND ADMINISTRATION: Renal Impairment in Adult Patients.) The serum half-life of aztreonam is only slightly prolonged in patients with hepatic impairment since the liver is a minor pathway of excretion.

Average urine concentrations of aztreonam were approximately 1100 mcg/mL, 3500 mcg/mL, and 6600 mcg/mL within the first 2 hours following single 500 mg, 1 g, and 2 g intravenous doses of AZACTAM (30-minute infusions), respectively. The range of average concentrations for aztreonam in the 8- to 12-hour urine specimens in these studies was 25 to 120 mcg/mL. After intramuscular injection of single 500 mg and 1 g doses of AZACTAM, urinary levels were approximately 500 mcg/mL and 1200 mcg/mL, respectively, within the first 2 hours, declining to 180 mcg/mL and 470 mcg/mL in the 6- to 8-hour specimens. In healthy subjects, aztreonam is excreted in the urine about equally by active tubular secretion and glomerular filtration. Approximately 60% to 70% of an intravenous or intramuscular dose was recovered in the urine by 8 hours. Urinary excretion of a single parenteral dose was essentially complete by 12 hours after injection. About 12% of a single intravenous radiolabeled dose was recovered in the feces. Unchanged aztreonam and the inactive beta-lactam ring hydrolysis product of aztreonam were present in feces and urine.

Intravenous or intramuscular administration of a single 500 mg or 1 g dose of AZACTAM every 8 hours for 7 days to healthy subjects produced no apparent accumulation of aztreonam or modification of its disposition characteristics; serum protein binding averaged 56% and was independent of dose. An average of about 6% of a 1 g intramuscular dose was excreted as a microbiologically inactive open beta-lactam ring hydrolysis product (serum half-life approximately 26 hours) of aztreonam in the 0‑ to 8-hour urine collection on the last day of multiple dosing.

Renal function was monitored in healthy subjects given aztreonam; standard tests (serum creatinine, creatinine clearance, BUN, urinalysis, and total urinary protein excretion) as well as special tests (excretion of N-acetyl-β-glucosaminidase, alanine aminopeptidase, and β2-microglobulin) were used. No abnormal results were obtained.

Aztreonam achieves measurable concentrations in the following body fluids and tissues:

Table 1: Extravascular Concentrations of Aztreonam After a Single Parenteral Dosea
Fluid or Tissue | Dose (g) | Route | Hours Post-injection | Number of Patients | Mean Concentration (mcg/mL or mcg/g)
Fluids
bile | 1 | IV | 2 | 10 | 39
blister fluid | 1 | IV | 1 | 6 | 20
bronchial secretion | 2 | IV | 4 | 7 | 5
cerebrospinal fluid (inflamed meninges) | 2 | IV | 0.9-4.3 | 16 | 3
pericardial fluid | 2 | IV | 1 | 6 | 33
pleural fluid | 2 | IV | 1.1-3.0 | 3 | 51
synovial fluid | 2 | IV | 0.8-1.9 | 11 | 83
Tissues
atrial appendage | 2 | IV | 0.9-1.6 | 12 | 22
endometrium | 2 | IV | 0.7-1.9 | 4 | 9
fallopian tube | 2 | IV | 0.7-1.9 | 8 | 12
fat | 2 | IV | 1.3-2.0 | 10 | 5
femur | 2 | IV | 1.0-2.1 | 15 | 16
gallbladder | 2 | IV | 0.8-1.3 | 4 | 23
kidney | 2 | IV | 2.4-5.6 | 5 | 67
large intestine | 2 | IV | 0.8-1.9 | 9 | 12
liver | 2 | IV | 0.9-2.0 | 6 | 47
lung | 2 | IV | 1.2-2.1 | 6 | 22
myometrium | 2 | IV | 0.7-1.9 | 9 | 11
ovary | 2 | IV | 0.7-1.9 | 7 | 13
prostate | 1 | IM | 0.8-3.0 | 8 | 8
skeletal muscle | 2 | IV | 0.3-0.7 | 6 | 16
skin | 2 | IV | 0.0-1.0 | 8 | 25
sternum | 2 | IV | 1 | 6 | 6
a Tissue penetration is regarded as essential to therapeutic efficacy, but specific tissue levels have not been correlated with specific therapeutic effects.

The concentration of aztreonam in saliva at 30 minutes after a single 1 g intravenous dose (9 patients) was 0.2 mcg/mL; in human milk at 2 hours after a single 1 g intravenous dose (6 patients), 0.2 mcg/mL, and at 6 hours after a single 1 g intramuscular dose (6 patients), 0.3 mcg/mL; in amniotic fluid at 6 to 8 hours after a single 1 g intravenous dose (5 patients), 2 mcg/mL. The concentration of aztreonam in peritoneal fluid obtained 1 to 6 hours after multiple 2 g intravenous doses ranged between 12 mcg/mL and 90 mcg/mL in 7 of 8 patients studied.

Aztreonam given intravenously rapidly reaches therapeutic concentrations in peritoneal dialysis fluid; conversely, aztreonam given intraperitoneally in dialysis fluid rapidly produces therapeutic serum levels.

Concomitant administration of probenecid or furosemide and aztreonam causes clinically insignificant increases in the serum levels of aztreonam. Single-dose intravenous pharmacokinetic studies have not shown any significant interaction between aztreonam and concomitantly administered gentamicin, nafcillin sodium, cephradine, clindamycin, or metronidazole. No reports of disulfiram-like reactions with alcohol ingestion have been noted; this is not unexpected since aztreonam does not contain a methyl-tetrazole side chain.

Microbiology

Mechanism of Action

Aztreonam is a bactericidal agent that acts by inhibition of bacterial cell wall synthesis. Aztreonam has activity in the presence of some beta-lactamases, both penicillinases and cephalosporinases, of Gram-negative and Gram-positive bacteria.

Mechanism of Resistance

Resistance to aztreonam is primarily through hydrolysis by beta-lactamase, alteration of penicillin-binding proteins (PBPs), and decreased permeability.

Interaction with Other Antimicrobials

Aztreonam and aminoglycosides have been shown to be synergistic in vitro against most strains of P. aeruginosa, many strains of Enterobacteriaceae, and other Gram-negative aerobic bacilli.

Aztreonam has been shown to be active against most strains of the following microorganisms, both in vitro and in clinical infections as described in the INDICATIONS AND USAGE section.

Aerobic Gram-negative microorganisms:

Citrobacter species

Enterobacter species

Escherichia coli

Haemophilus influenzae (including ampicillin-resistant and other penicillinase-producing strains)

Klebsiella oxytoca

Klebsiella pneumoniae

Proteus mirabilis

Pseudomonas aeruginosa

Serratia species

The following in vitro data are available, but their clinical significance is unknown. At least 90% of the following microorganisms exhibit an in vitro minimum inhibitory concentration (MIC) less than or equal to the susceptible breakpoint for aztreonam. However, the efficacy of aztreonam in treating clinical infections due to these microorganisms has not been established in adequate and well-controlled clinical trials.

Aerobic Gram-negative microorganisms:

Aeromonas hydrophila

Morganella morganii

Neisseria gonorrhoeae (including penicillinase-producing strains)

Pasteurella multocida Proteus vulgaris

Providencia stuartii

Providencia rettgeri

Yersinia enterocolitica

Aztreonam and aminoglycosides have been shown to be synergistic in vitro against most strains of P. aeruginosa, many strains of Enterobacteriaceae, and other Gram-negative aerobic bacilli.

Alterations of the anaerobic intestinal flora by broad-spectrum antibiotics may decrease colonization resistance, thus permitting overgrowth of potential pathogens, eg, Candida and Clostridium species. Aztreonam has little effect on the anaerobic intestinal microflora in in vitro studies. Clostridium difficile and its cytotoxin were not found in animal models following administration of aztreonam. (See ADVERSE REACTIONS: Gastrointestinal.)

Susceptibility Testing

For specific information regarding susceptibility test interpretive criteria and associated test methods and quality control standards recognized by FDA for this drug, please see: https://www.fda.gov/STIC.

INDICATIONS AND USAGE

To reduce the development of drug-resistant bacteria and maintain the effectiveness of AZACTAM (aztreonam for injection, USP) and other antibacterial drugs, AZACTAM should be used only to treat or prevent infections that are proven or strongly suspected to be caused by susceptible bacteria. When culture and susceptibility information are available, they should be considered in selecting or modifying antibacterial therapy. In the absence of such data, local epidemiology and susceptibility patterns may contribute to the empiric selection of therapy.

AZACTAM is indicated for the treatment of the following infections caused by susceptible Gram-negative microorganisms:

Urinary Tract Infections (complicated and uncomplicated), including pyelonephritis and cystitis (initial and recurrent) caused by Escherichia coli, Klebsiella pneumoniae, Proteus mirabilis, Pseudomonas aeruginosa, Enterobacter cloacae, Klebsiella oxytoca*, Citrobacter species*, and Serratia marcescens*.

Lower Respiratory Tract Infections, including pneumonia and bronchitis caused by Escherichia coli, Klebsiella pneumoniae, Pseudomonas aeruginosa, Haemophilus influenzae, Proteus mirabilis, Enterobacter species, and Serratia marcescens*.

Septicemia caused by Escherichia coli, Klebsiella pneumoniae, Pseudomonas aeruginosa, Proteus mirabilis*, Serratia marcescens*, and Enterobacter species.

Skin and Skin-Structure Infections, including those associated with postoperative wounds, ulcers, and burns, caused by Escherichia coli, Proteus mirabilis, Serratia marcescens, Enterobacter species, Pseudomonas aeruginosa, Klebsiella pneumoniae, and Citrobacter species*.

Intra-abdominal Infections, including peritonitis caused by Escherichia coli, Klebsiella species including K. pneumoniae, Enterobacter species including E. cloacae*, Pseudomonas aeruginosa, Citrobacter species* including C. freundii*, and Serratia species* including S. marcescens*.

Gynecologic Infections, including endometritis and pelvic cellulitis caused by Escherichia coli, Klebsiella pneumoniae*, Enterobacter species* including E. cloacae*, and Proteus mirabilis*.

AZACTAM is indicated for adjunctive therapy to surgery in the management of infections caused by susceptible organisms, including abscesses, infections complicating hollow viscus perforations, cutaneous infections, and infections of serous surfaces. AZACTAM is effective against most of the commonly encountered Gram-negative aerobic pathogens seen in general surgery.

-------------------------------

* Efficacy for this organism in this organ system was studied in fewer than 10 infections.

Concurrent Therapy

Concurrent initial therapy with other antimicrobial agents and AZACTAM is recommended before the causative organism(s) is known in seriously ill patients who are also at risk of having an infection due to Gram-positive aerobic pathogens. If anaerobic organisms are also suspected as etiologic agents, therapy should be initiated using an anti-anaerobic agent concurrently with AZACTAM (see DOSAGE AND ADMINISTRATION). Certain antibiotics (eg, cefoxitin, imipenem) may induce high levels of beta-lactamase in vitro in some Gram-negative aerobes such as Enterobacter and Pseudomonas species, resulting in antagonism to many beta-lactam antibiotics including aztreonam. These in vitro findings suggest that such beta-lactamase-inducing antibiotics not be used concurrently with aztreonam. Following identification and susceptibility testing of the causative organism(s), appropriate antibiotic therapy should be continued.

CONTRAINDICATIONS

This preparation is contraindicated in patients with known hypersensitivity to aztreonam or any other component in the formulation.

WARNINGS

Both animal and human data suggest that AZACTAM (aztreonam for injection, USP) is rarely cross-reactive with other beta-lactam antibiotics and weakly immunogenic. Treatment with aztreonam can result in hypersensitivity reactions in patients with or without prior exposure. (See CONTRAINDICATIONS.)

Careful inquiry should be made to determine whether the patient has any history of hypersensitivity reactions to any allergens.

While cross-reactivity of aztreonam with other beta-lactam antibiotics is rare, this drug should be administered with caution to any patient with a history of hypersensitivity to beta-lactams (eg, penicillins, cephalosporins, and/or carbapenems). Treatment with aztreonam can result in hypersensitivity reactions in patients with or without prior exposure to aztreonam. If an allergic reaction to aztreonam occurs, discontinue the drug and institute supportive treatment as appropriate (eg, maintenance of ventilation, pressor amines, antihistamines, corticosteroids). Serious hypersensitivity reactions may require epinephrine and other emergency measures. (See ADVERSE REACTIONS.)

Clostridium difficile–associated diarrhea (CDAD) has been reported with use of nearly all antibacterial agents, including AZACTAM, and may range in severity from mild diarrhea to fatal colitis. Treatment with antibacterial agents alters the normal flora of the colon leading to overgrowth of C. difficile.

C. difficile produces toxins A and B which contribute to the development of CDAD. Hypertoxin-producing strains of C. difficile cause increased morbidity and mortality, as these infections can be refractory to antimicrobial therapy and may require colectomy. CDAD must be considered in all patients who present with diarrhea following antibiotic use. Careful medical history is necessary since CDAD has been reported to occur over 2 months after the administration of antibacterial agents.

If CDAD is suspected or confirmed, ongoing antibiotic use not directed against C. difficile may need to be discontinued. Appropriate fluid and electrolyte management, protein supplementation, antibiotic treatment of C. difficile, and surgical evaluation should be instituted as clinically indicated.

Rare cases of toxic epidermal necrolysis have been reported in association with aztreonam in patients undergoing bone marrow transplant with multiple risk factors including sepsis, radiation therapy, and other concomitantly administered drugs associated with toxic epidermal necrolysis.

PRECAUTIONS

General

Prescribing AZACTAM in the absence of a proven or strongly suspected bacterial infection or a prophylactic indication is unlikely to provide benefit to the patient and increases the risk of the development of drug-resistant bacteria.

In patients with impaired hepatic or renal function, appropriate monitoring is recommended during therapy.

If an aminoglycoside is used concurrently with aztreonam, especially if high dosages of the former are used or if therapy is prolonged, renal function should be monitored because of the potential nephrotoxicity and ototoxicity of aminoglycoside antibiotics.

The use of antibiotics may promote the overgrowth of nonsusceptible organisms, including Gram-positive organisms (Staphylococcus aureus and Streptococcus faecalis) and fungi. Should superinfection occur during therapy, appropriate measures should be taken.

Information for Patients

Patients should be counseled that antibacterial drugs including AZACTAM should only be used to treat bacterial infections. They do not treat viral infections (eg, the common cold). When AZACTAM is prescribed to treat a bacterial infection, patients should be told that although it is common to feel better early in the course of therapy, the medication should be taken exactly as directed. Skipping doses or not completing the full course of therapy may (1) decrease the effectiveness of the immediate treatment and (2) increase the likelihood that bacteria will develop resistance and will not be treatable by AZACTAM or other antibacterial drugs in the future.

Diarrhea is a common problem caused by antibiotics which usually ends when the antibiotic is discontinued. Sometimes after starting treatment with antibiotics, patients can develop watery and bloody stools (with or without stomach cramps and fever) even as late as 2 or more months after having taken the last dose of the antibiotic. If this occurs, patients should contact their physician as soon as possible.

Carcinogenesis, Mutagenesis, Impairment of Fertility

Carcinogenicity studies with aztreonam have not been conducted using an intravenous route of administration. A 104-week rat inhalation toxicology study to assess the carcinogenic potential of aztreonam demonstrated no drug-related increase in the incidence of tumors. Rats were exposed to aerosolized aztreonam for up to 4 hours per day. Peak plasma levels of aztreonam averaging approximately 6.8 mcg/mL were measured in rats at the highest dose level.

Genetic toxicology studies performed with aztreonam in vitro (Ames test, mouse lymphoma forward mutation assay, gene conversion assay, chromosome aberration assay in human lymphocytes) and in vivo (mouse bone marrow cytogenetic assay) did not reveal evidence of mutagenic or clastogenic potential.

A two-generation reproduction study in rats at daily doses of 150, 600, or 2400 mg/kg given prior to and during gestation and lactation, revealed no evidence of impaired fertility. Based on body surface area, the high dose is 2.9-fold greater than the maximum recommended human dose (MRHD) for adults of 8 g per day. There was a slightly reduced survival rate during the lactation period in the offspring of rats that received the highest dose, but not in offspring of rats that received lower doses of aztreonam.

Pregnancy

In pregnant women, aztreonam crosses the placenta and enters the fetal circulation.

Developmental toxicity studies in pregnant rats and rabbits with daily doses of aztreonam up to 1800 and 1200 mg/kg, respectively, revealed no evidence of embryotoxicity or fetotoxicity or teratogenicity. These doses, based on body surface area, are 2.2- and 2.9-fold greater than the MRHD for adults of 8 g per day. A peri/postnatal study in rats revealed no drug-induced changes in any maternal, fetal, or neonatal parameters. The highest dose used in this study, 1800 mg/kg/day, is 2.2 times the MRHD based on body surface area.

There are no adequate and well-controlled studies of aztreonam on human pregnancy outcomes. Because animal reproduction studies are not always predictive of human response, aztreonam should be used during pregnancy only if clearly needed.

Nursing Mothers

Aztreonam is excreted in human milk in concentrations that are less than 1% of concentrations determined in simultaneously obtained maternal serum; consideration should be given to temporary discontinuation of nursing and use of formula feedings.

Pediatric Use

The safety and effectiveness of intravenous AZACTAM have been established in the age groups 9 months to 16 years. Use of AZACTAM in these age groups is supported by evidence from adequate and well-controlled studies of AZACTAM in adults with additional efficacy, safety, and pharmacokinetic data from noncomparative clinical studies in pediatric patients. Sufficient data are not available for pediatric patients under 9 months of age or for the following treatment indications/pathogens: septicemia and skin and skin-structure infections (where the skin infection is believed or known to be due to H. influenzae type b). In pediatric patients with cystic fibrosis, higher doses of AZACTAM may be warranted. (See CLINICAL PHARMACOLOGY, DOSAGE AND ADMINISTRATION, and CLINICAL STUDIES.)

Geriatric Use

Clinical studies of AZACTAM did not include sufficient numbers of subjects aged 65 years and over to determine whether they respond differently from younger subjects. Other reported clinical experience has not identified differences in responses between the elderly and younger patients. In general, dose selection for an elderly patient should be cautious, reflecting the greater frequency of decreased hepatic, renal, or cardiac function, and of concomitant disease or other drug therapy.

In elderly patients, the mean serum half-life of aztreonam increased and the renal clearance decreased, consistent with the age-related decrease in creatinine clearance. Since aztreonam is known to be substantially excreted by the kidney, the risk of toxic reactions to this drug may be greater in patients with impaired renal function. Because elderly patients are more likely to have decreased renal function, renal function should be monitored and dosage adjustments made accordingly (see DOSAGE AND ADMINISTRATION: Renal Impairment in Adult Patients and Dosage in the Elderly).

AZACTAM contains no sodium.

ADVERSE REACTIONS

Local reactions such as phlebitis/thrombophlebitis following intravenous administration, and discomfort/swelling at the injection site following intramuscular administration occurred at rates of approximately 1.9% and 2.4%, respectively.

Systemic reactions (considered to be related to therapy or of uncertain etiology) occurring at an incidence of 1% to 1.3% include diarrhea, nausea and/or vomiting, and rash. Reactions occurring at an incidence of less than 1% are listed within each body system in order of decreasing severity:

Hypersensitivity—anaphylaxis, angioedema, bronchospasm

Hematologic—pancytopenia, neutropenia, thrombocytopenia, anemia, eosinophilia, leukocytosis, thrombocytosis

Gastrointestinal—abdominal cramps; rare cases of C. difficile–associated diarrhea, including pseudomembranous colitis, or gastrointestinal bleeding have been reported. Onset of pseudomembranous colitis symptoms may occur during or after antibiotic treatment. (See WARNINGS.)

Dermatologic—toxic epidermal necrolysis (see WARNINGS), purpura, erythema multiforme, exfoliative dermatitis, urticaria, petechiae, pruritus, diaphoresis

Cardiovascular—hypotension, transient ECG changes (ventricular bigeminy and PVC), flushing

Respiratory—wheezing, dyspnea, chest pain

Hepatobiliary—hepatitis, jaundice

Nervous System—seizure, confusion, encephalopathy, vertigo, paresthesia, insomnia, dizziness

Musculoskeletal—muscular aches

Special Senses—tinnitus, diplopia, mouth ulcer, altered taste, numb tongue, sneezing, nasal congestion, halitosis

Other—vaginal candidiasis, vaginitis, breast tenderness

Body as a Whole—weakness, headache, fever, malaise

Pediatric Adverse Reactions

Of the 612 pediatric patients who were treated with AZACTAM in clinical trials, less than 1% required discontinuation of therapy due to adverse events. The following systemic adverse events, regardless of drug relationship, occurred in at least 1% of treated patients in domestic clinical trials: rash (4.3%), diarrhea (1.4%), and fever (1.0%). These adverse events were comparable to those observed in adult clinical trials.

In 343 pediatric patients receiving intravenous therapy, the following local reactions were noted: pain (12%), erythema (2.9%), induration (0.9%), and phlebitis (2.1%). In the US patient population, pain occurred in 1.5% of patients, while each of the remaining 3 local reactions had an incidence of 0.5%.

The following laboratory adverse events, regardless of drug relationship, occurred in at least 1% of treated patients: increased eosinophils (6.3%), increased platelets (3.6%), neutropenia (3.2%), increased AST (3.8%), increased ALT (6.5%), and increased serum creatinine (5.8%).

In US pediatric clinical trials, neutropenia (absolute neutrophil count less than 1000/mm^3) occurred in 11.3% of patients (8/71) younger than 2 years receiving 30 mg/kg every 6 hours. AST and ALT elevations to greater than 3 times the upper limit of normal were noted in 15% to 20% of patients aged 2 years or above receiving 50 mg/kg every 6 hours. The increased frequency of these reported laboratory adverse events may be due to either increased severity of illness treated or higher doses of AZACTAM administered.

Adverse laboratory changes without regard to drug relationship that were reported during clinical trials were:

Hepatic—elevations of AST (SGOT), ALT (SGPT), and alkaline phosphatase; signs or symptoms of hepatobiliary dysfunction occurred in less than 1% of recipients (see above).

Hematologic—increases in prothrombin and partial thromboplastin times, positive Coombs’ test.

Renal—increases in serum creatinine.

OVERDOSAGE

If necessary, aztreonam may be cleared from the serum by hemodialysis and/or peritoneal dialysis.

DOSAGE AND ADMINISTRATION

Dosage in Adult Patients

AZACTAM may be administered intravenously or by intramuscular injection. Dosage and route of administration should be determined by susceptibility of the causative organisms, severity and site of infection, and the condition of the patient.

Table 2: AZACTAM Dosage Guidelines for Adults*
Type of Infection | Dose | Frequency; (hours)
Urinary tract infections | 500 mg or 1 g | 8 or 12
Moderately severe systemic infections | 1 g or 2 g | 8 or 12
Severe systemic or life-threatening infections | 2 g | 6 or 8
* Maximum recommended dose is 8 g per day.

Because of the serious nature of infections due to Pseudomonas aeruginosa, dosage of 2 g every six or eight hours is recommended, at least upon initiation of therapy, in systemic infections caused by this organism.

The intravenous route is recommended for patients requiring single doses greater than 1 g or those with bacterial septicemia, localized parenchymal abscess (eg, intra-abdominal abscess), peritonitis, or other severe systemic or life-threatening infections.

The duration of therapy depends on the severity of infection. Generally, AZACTAM should be continued for at least 48 hours after the patient becomes asymptomatic or evidence of bacterial eradication has been obtained. Persistent infections may require treatment for several weeks. Doses smaller than those indicated should not be used.

Renal Impairment in Adult Patients

Prolonged serum levels of aztreonam may occur in patients with transient or persistent renal insufficiency. Therefore, the dosage of AZACTAM should be halved in patients with estimated creatinine clearances between 10 and 30 mL/min/1.73 m^2 after an initial loading dose of 1g or 2 g.

When only the serum creatinine concentration is available, the following formula (based on sex, weight, and age of the patient) may be used to approximate the creatinine clearance (ClCr). The serum creatinine should represent a steady state of renal function.

In patients with severe renal failure (creatinine clearance less than 10 mL/min/1.73 m^2), such as those supported by hemodialysis, the usual dose of 500 mg, 1 g, or 2 g should be given initially. The maintenance dose should be one-fourth of the usual initial dose given at the usual fixed interval of 6, 8, or 12 hours. For serious or life-threatening infections, in addition to the maintenance doses, one-eighth of the initial dose should be given after each hemodialysis session.

Dosage in the Elderly

Renal status is a major determinant of dosage in the elderly; these patients in particular may have diminished renal function. Serum creatinine may not be an accurate determinant of renal status. Therefore, as with all antibiotics eliminated by the kidneys, estimates of creatinine clearance should be obtained and appropriate dosage modifications made if necessary.

Dosage in Pediatric Patients

AZACTAM should be administered intravenously to pediatric patients with normal renal function. There are insufficient data regarding intramuscular administration to pediatric patients or dosing in pediatric patients with renal impairment. (See PRECAUTIONS: Pediatric Use.)

Table 3: AZACTAM Dosage Guidelines for Pediatric Patients*
Type of Infection | Dose | Frequency; (hours)
Mild to moderate infections | 30 mg/kg | 8
Moderate to severe infections | 30 mg/kg | 6 or 8
* Maximum recommended dose is 120 mg/kg/day.

CLINICAL STUDIES

A total of 612 pediatric patients aged 1 month to 12 years were enrolled in uncontrolled clinical trials of aztreonam in the treatment of serious Gram-negative infections, including urinary tract, lower respiratory tract, skin and skin-structure, and intra-abdominal infections.

Preparation of Parenteral Solutions

General

Upon the addition of the diluent to the container, contents should be shaken immediately and vigorously. Use constituted solution immediately. Discard any remaining unused constituted solution.

Depending upon the concentration of aztreonam and diluent used, constituted AZACTAM yields a colorless to light straw yellow solution which may develop a slight pink tint on standing (potency is not affected). Parenteral drug products should be inspected visually for particulate matter and discoloration whenever solution and container permit.

Admixtures with Other Antibiotics

Intravenous infusion solutions of AZACTAM not exceeding 2% w/v prepared with Sodium Chloride Injection, USP 0.9% or Dextrose Injection, USP 5%, to which clindamycin phosphate, gentamicin sulfate, tobramycin sulfate, or cefazolin sodium have been added at concentrations usually used clinically, are stable for up to 48 hours at controlled room temperature 15°C to 30°C (59°F to 86°F) or 7 days under refrigeration 2°C to 8°C (36°F to 46°F). Ampicillin sodium admixtures with aztreonam in Sodium Chloride Injection, USP 0.9% are stable for 24 hours at controlled room temperature 15°C to 30°C (59°F to 86°F) and 48 hours under refrigeration 2°C to 8°C (36°F to 46°F); stability in Dextrose Injection, USP 5% is 2 hours at controlled room temperature 15°C to 30°C (59°F to 86°F) and 8 hours under refrigeration 2°C to 8°C (36°F to 46°F).

Aztreonam-cloxacillin sodium and aztreonam-vancomycin hydrochloride admixtures are stable in Dianeal 137 (Peritoneal Dialysis Solution) with 4.25% Dextrose for up to 24 hours at controlled room temperature 15°C to 30°C (59°F to 86°F).

Aztreonam is incompatible with nafcillin sodium, cephradine, and metronidazole.

Other admixtures are not recommended since compatibility data are not available.

Intravenous Solutions

For Bolus Injection: The vial contents should be constituted with 6 mL to 10 mL Sterile Water for Injection, USP.

For Infusion: If the vial contents are to be transferred to an appropriate infusion solution, each gram of aztreonam should be initially constituted with at least 3 mL Sterile Water for Injection, USP. Further dilution may be obtained with one of the following intravenous infusion solutions:

Sodium Chloride Injection, USP, 0.9%

Ringer’s Injection, USP

Lactated Ringer’s Injection, USP

Dextrose Injection, USP, 5% or 10%

Dextrose and Sodium Chloride Injection, USP, 5%:0.9%, 5%:0.45%, or 5%:0.2%

Sodium Lactate Injection, USP (M/6 Sodium Lactate)

Ionosol® B and 5% Dextrose

Isolyte® E

Isolyte® E with 5% Dextrose

Isolyte® M with 5% Dextrose

Normosol®-R

Normosol®-R and 5% Dextrose

Normosol®-M and 5% Dextrose

Mannitol Injection, USP, 5% or 10%

Lactated Ringer’s and 5% Dextrose Injection

Plasma-Lyte M and 5% Dextrose

Intramuscular Solutions

The vial contents should be constituted with at least 3 mL of an appropriate diluent per gram aztreonam. The following diluents may be used:

Sterile Water for Injection, USP

Sterile Bacteriostatic Water for Injection, USP (with benzyl alcohol or with methyl- and propylparabens)

Sodium Chloride Injection, USP, 0.9%

Bacteriostatic Sodium Chloride Injection, USP (with benzyl alcohol)

Stability of Intravenous and Intramuscular Solutions

AZACTAM solutions for intravenous infusion at concentrations not exceeding 2% w/v must be used within 48 hours following constitution if kept at controlled room temperature 15°C to 30°C (59°F to 86°F) or within 7 days if refrigerated 2°C to 8°C (36°F to 46°F).

AZACTAM solutions at concentrations exceeding 2% w/v, except those prepared with Sterile Water for Injection, USP or Sodium Chloride Injection, USP, should be used promptly after preparation; the 2 excepted solutions must be used within 48 hours if stored at controlled room temperature 15°C to 30°C (59°F to 86°F) or within 7 days if refrigerated 2°C to 8°C (36°F to 46°F).

Intravenous Administration

Bolus Injection: A bolus injection may be used to initiate therapy. The dose should be slowly injected directly into a vein, or the tubing of a suitable administration set, over a period of 3 to 5 minutes (see next paragraph regarding flushing of tubing).

Infusion: With any intermittent infusion of aztreonam and another drug with which it is not pharmaceutically compatible, the common delivery tube should be flushed before and after delivery of aztreonam with any appropriate infusion solution compatible with both drug solutions; the drugs should not be delivered simultaneously. Any AZACTAM infusion should be completed within a 20- to 60-minute period. With use of a Y-type administration set, careful attention should be given to the calculated volume of aztreonam solution required so that the entire dose will be infused. A volume control administration set may be used to deliver an initial dilution of AZACTAM (see Preparation of Parenteral Solutions: Intravenous Solutions: For Infusion) into a compatible infusion solution during administration; in this case, the final dilution of aztreonam should provide a concentration not exceeding 2% w/v.

Intramuscular Administration

The dose should be given by deep injection into a large muscle mass (such as the upper outer quadrant of the gluteus maximus or lateral part of the thigh). Aztreonam is well tolerated and should not be admixed with any local anesthetic agent.

HOW SUPPLIED

AZACTAM® (aztreonam for injection, USP)

Single-dose vials:

- 1 gram/vial: | Packages of 10 | NDC 0003-2560-16
- 2 grams/vial: | Packages of 10 | NDC 0003-2570-16

Storage

Store in original package at 20°C to 25°C (68°F to 77°F) [see USP controlled room temperature]; avoid excessive heat.

AZACTAM and the Bristol-Myers Squibb logo are registered trademarks of Bristol-Myers Squibb Company.

All other trademarks are the property of their respective owners.

Manufactured by:
Bristol-Myers Squibb Company
Princeton, NJ 08543 USA

Revised: March 2023

PACKAGE/LABEL PRINCIPAL DISPLAY PANEL

REPRESENTATIVE PACKAGING

See HOW SUPPLIED section for a complete list of available packages of AZACTAM.

NDC 0003-2560-16
1 gram
AZACTAM®
(aztreonam for injection, USP)

FOR INTRAVENOUS
OR
INTRAMUSCULAR USE

Single-Dose vial - Discard Unused Portion

Rx only
Bristol-Myers Squibb

PACKAGE/LABEL PRINCIPAL DISPLAY PANEL

NDC 0003-2570-16
2 grams
AZACTAM®
(aztreonam for injection, USP)

FOR INTRAVENOUS
OR
INTRAMUSCULAR USE

Single-Dose vial - Discard Unused Portion

Rx only
Bristol-Myers Squibb